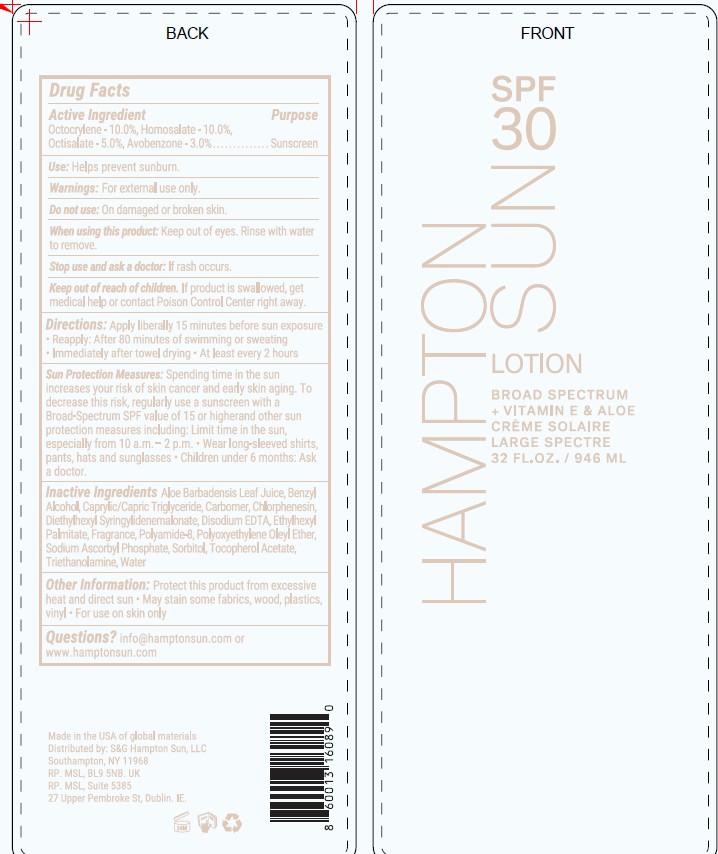 DRUG LABEL: Broad Spectrum Sunscreen SPF 30
NDC: 87170-007 | Form: LOTION
Manufacturer: S&C Hampton Sun LLC
Category: otc | Type: HUMAN OTC DRUG LABEL
Date: 20260127

ACTIVE INGREDIENTS: OCTOCRYLENE 10 mg/100 mL; HOMOSALATE 10 mg/100 mL; OCTISALATE 5 mg/100 mL; AVOBENZONE 3 mg/100 mL
INACTIVE INGREDIENTS: SORBITOL; .ALPHA.-TOCOPHEROL ACETATE; TRIETHANOLAMINE; WATER; ALOE; BENZYL ALCOHOL; CAPRYLIC/CAPRIC TRIGLYCERIDE; CARBOMER; CHLORPHENESIN; DIETHYLHEXYL SYRINGYLIDENEMALONATE; EDETATE DISODIUM; ETHYLHEXYL PALMITATE; FRAGRANCE ESC 10-740; POLYAMIDE-8 (4500 MW); OLETH-20; SODIUM ASCORBYL PHOSPHATE

Hampton Sun SPF 30 Broad Spectrum Sunscreen Lotion (IS0022-AL)

Active Ingredeints Purpose

Octocrylene - 10.00 % Sunscreen
Homosalate - 10.00 % Sunscreen
octisalate - 5-00 % Sunscreen
AvohenTone 3 00 % Sunscreen

Uses

Uses ■ helps prevent sunburn

Keep out of reach of children.

if swallowed, get medical help or contact a Polson Control Center right away.

Warnings For external use only.

Flammable: Do not use white smoking or near heat or flame.
Do not useon damaged or broken skin.
When using this product■ keep out of eyes. Rinse eyes with water to remove.
Stop use and ask a doctor ifrash occurs.

Directions

Directions apply liberally to cool, dry skin
15 minutes before sun exposure • reapply:
• after 80 minutes of swimming or sweating
• immediately after towel drying • at least every 2
hours • Sun Protection Measures. Spending time
in the sun increases your risk of skin cancer and
early skin aging. To decrease this risk, regularly
use a sunscreen with a broad spectrum SPF of 15
or higher and other sun protection measures
including: • limit time in the sun,especially from
10 a.m. - 2. p.m. • wear a long-sleeve shirts,
pants, hats, and sunglasses. • children under 6
months: Ask a doctor.

Ingredients

Aloe Barbadensis Leaf Juice
BenzvlAlcohol
Caprylic/Capric TrigLyceride
carbomer
Chlorphenesin
Diethylhexyl
Svrinsvlidenemalonate
Disodium EDTA
EthvlhexvlPalmitate
Fragrance
Polyamide 8
Polyoxyethylene Oleyl Ether
Sodium Ascorbyl Phosphate
Sorbitol
TocopherolAcetate
Triethanolamine